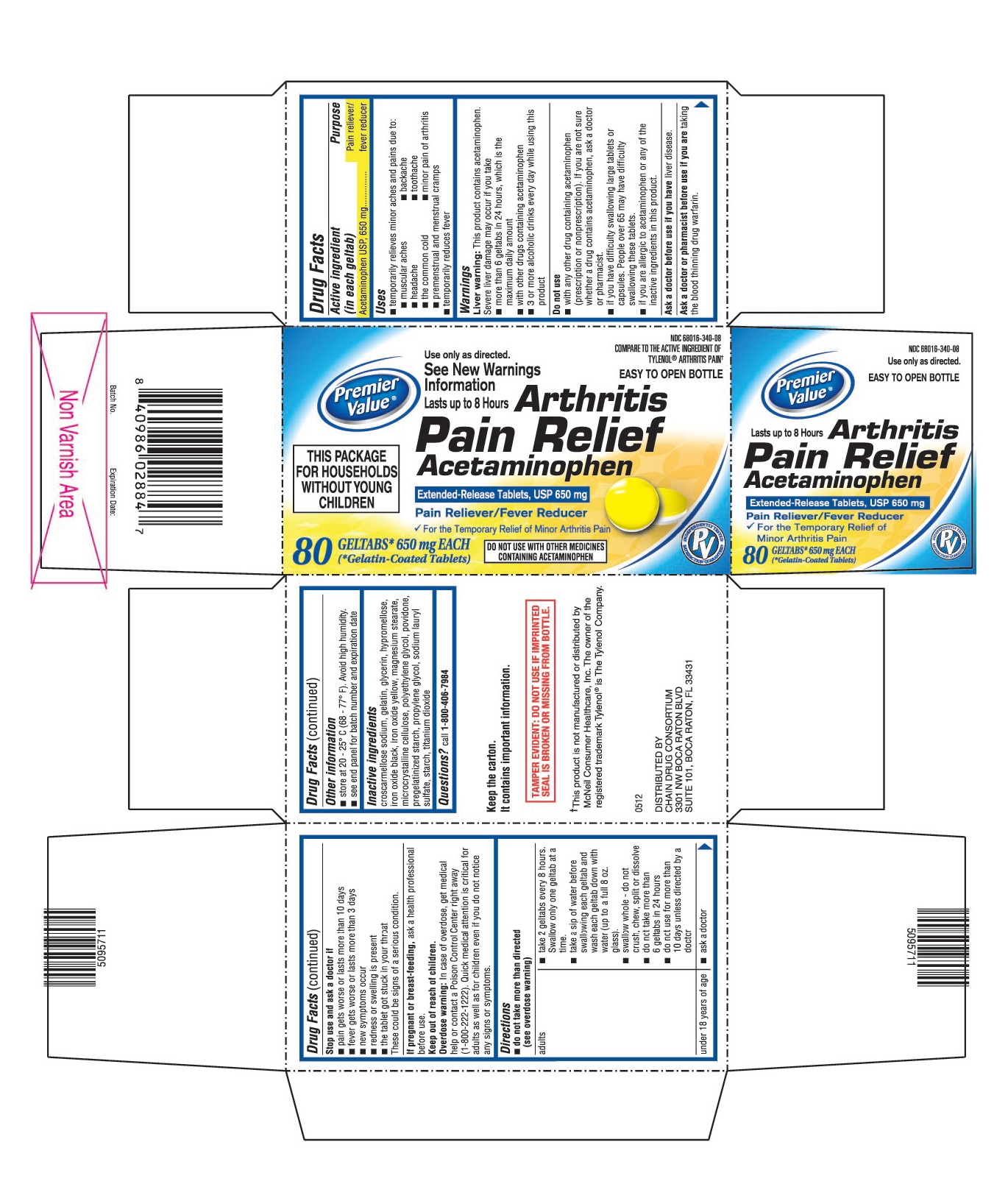 DRUG LABEL: Premier Value Arthritis Pain Reliever
NDC: 68016-340 | Form: TABLET, EXTENDED RELEASE
Manufacturer: Chain Drug Consortium, LLC
Category: otc | Type: HUMAN OTC DRUG LABEL
Date: 20151005

ACTIVE INGREDIENTS: ACETAMINOPHEN 650 mg/1 1
INACTIVE INGREDIENTS: CROSCARMELLOSE SODIUM; GELATIN; GLYCERIN; HYPROMELLOSES; FERROSOFERRIC OXIDE; FERRIC OXIDE YELLOW; MAGNESIUM STEARATE; CELLULOSE, MICROCRYSTALLINE; POLYETHYLENE GLYCOLS; STARCH, CORN; SODIUM LAURYL SULFATE; TITANIUM DIOXIDE; POVIDONES

Drug Facts

ACTIVE INGREDIENT (IN EACH GELTAB)

Acetaminophen USP, 650 mg

PURPOSE

Pain reliever/fever reducer

USES

- temporarily relieves minor aches and pains due to:
  - muscular aches
  - backache
  - headache
  - toothache
  - the common cold
  - minor pain of arthritis
  - premenstrual and menstrual cramps
- temporarily reduces fever

WARNINGS

Liver warning: This product contains acetaminophen. Severe liver damage may occur if you take

- more than 6 geltabs in 24 hours, which is the maximum daily amount
- with other drugs containing acetaminophen
- 3 or more alcoholic drinks every day while using this product

Do not use

- with any other drug containing acetaminophen (prescription or nonprescription). If you are not sure whether a drug contains acetaminophen, ask a doctor or pharmacist.
- if you have difficulty swallowing large tablets or capsules. People over 65 may have difficulty swallowing these tablets.
- if you are allergic to acetaminophen or any of the inactive ingredients in this product.

Ask a doctor before use if you have

Liver disease.

Ask a doctor or pharmacist before use if you are

Taking the blood thinning drug warfarin.

Stop use and ask a doctor if

- pain gets worse or lasts more than 10 days
- fever gets worse or lasts more than 3 days
- new symptoms occur
- redness or swelling is present
- the tablet got stuck in your throat

These could be signs of a serious condition.

If pregnant or breast-feeding

Ask a health professional before use.

Keep out of reach of children.

Overdose warning: In case of overdose, get medical help or contact a Poison Control Center right away (1-800-222-1222). Quick medical attention is critical for adults as well as for children even if you do not notice any signs or symptoms.

DIRECTIONS

- do not take more than directed (see overdose warning)

adults | ▪ take 2 geltabs every 8 hours. Swallow only one geltab at a time. ▪ take a sip of water before swallowing each geltab and wash each geltab down with water (up to a full 8 oz. glass). ▪ swallow whole - do not crush, chew, split or dissolve ▪ do not take more than 6 geltabs in 24 hours ▪ do not use for more than 10 days unless directed by a doctor
under 18 years of age | ▪ ask a doctor

OTHER INFORMATION

- store at 20 - 25° C (68 - 77° F). Avoid high humidity.
- see end panel for batch number and expiration date
- TAMPER EVIDENT: DO NOT USE IF IMPRINTED SEAL IS BROKEN OR MISSING FROM BOTTLE.

INACTIVE INGREDIENTS

Croscarmellose sodium, gelatin, glycerin, hypromellose, iron oxide black, iron oxide yellow, magnesium stearate, microcrystalline cellulose, polyethylene glycol, povidone, pregelatinized starch, propylene glycol, sodium lauryl sulfate, starch, titanium dioxide

QUESTIONS?

Call 1-800-406-7984

PRINCIPAL DISPLAY PANEL

Premier Value®

NDC 68016-340-08

Use only as directed.

See New Warnings Information

EASY TO OPEN BOTTLE

Lasts up to 8 hours

Arthritis Pain Relief

Acetaminophen Extended-Release Tablets, USP 650 mg

Pain Reliever/Fever Reducer

For the Temporary Relief of Minor Arthritis Pain

THIS PACKAGE FOR HOUSEHOLDS WITHOUT YOUNG CHILDREN

DO NOT USE WITH OTHER MEDICINES CONTAINING ACETAMINOPHEN

80 GELTABS* 650 mg EACH

(* Gelatin-Coated Tablets)

COMPARE TO THE ACTIVE INGREDIENT OF TYLENOL® ARTHRITIS PAIN†

DISTRIBUTED BY CHAIN DRUG CONSORTIUM

5095711/0512